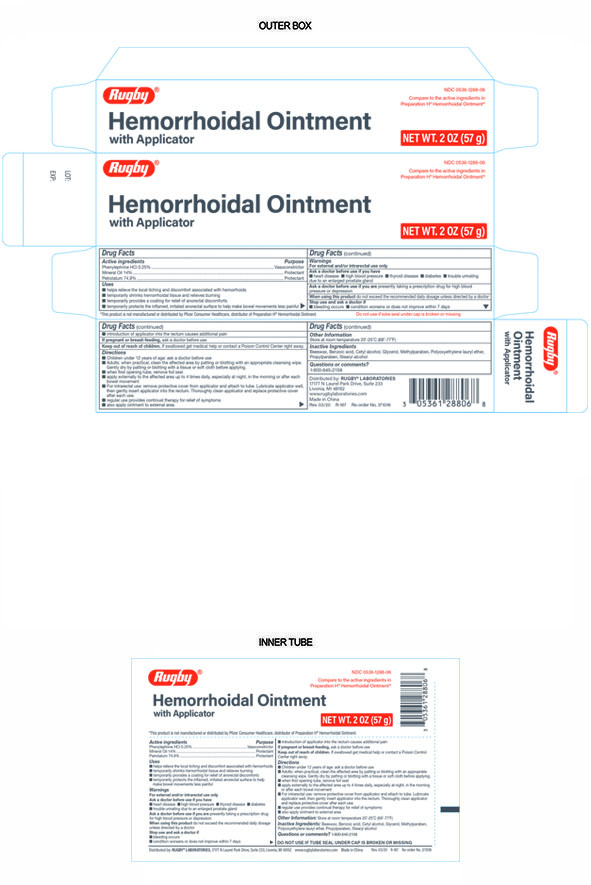 DRUG LABEL: Hemorrhoidal
NDC: 0536-1288 | Form: OINTMENT
Manufacturer: Rugby
Category: otc | Type: HUMAN OTC DRUG LABEL
Date: 20241217

ACTIVE INGREDIENTS: PHENYLEPHRINE HYDROCHLORIDE 0.25 g/100 g; MINERAL OIL 14 g/100 g; PETROLATUM 74.9 g/100 g
INACTIVE INGREDIENTS: STEARYL ALCOHOL; BENZOIC ACID; CETYL ALCOHOL; LAURETH-23; METHYLPARABEN; YELLOW WAX; GLYCERIN; PROPYLPARABEN

Hemorrhoidal Ointment

Active Ingredient

Phenylephrine HCI 0.25%

Purpose

Vasoconstrictor

Active Ingredient

Mineral Oil 14%

Purpose

Protectant

Active Ingredient

Petrolatum 74.9%

Purpose

Protectant

Uses

- Helps relieve the local itching and discomfort associated with hemorrhoids
- Temporarily shrinks hemorrhoidal tissue and relieves burning
- Temporarily provides a coating for relief of anorectal discomforts
- Temporarily protects the inflamed, irritated anorectal surface to help make bowel movements less painful

Warnings

For external and/or intrarectal use only

Ask doctor before use if you have

heart disease

high blood pressure

thyroid disease

diabetes

trouble urinating due to an enlarged prostate gland

Ask doctor before use if you are presently taking a prescription drug for high blood pressure or depression.

Stop Use and Ask Doctor if

- Bleeding occurs
- Condition worsens or does not improve within 7 days
- Introduction of applicator into the rectum causes additional pain

If Pregnant or breast-feeding

Ask a doctor before use

Keep out of reach of children

If swallowed get medical help or contact a Poison Control Center right away.

Directions

- Children under 12 years of age; ask doctor before use
- Adults: when practical, clean the affected area by patting or blotting with an appropriate cleansing wipe.

Gently dry by patting or blotting with a tissue or soft cloth before applying.

- When first opening tube, remove foil seal
- Apply externally to the affected area up to 4 times daily, especially at night, in the morning or after each bowel movement.
- For intrarectal use: remove protective cover from applicator and attach to tube. Lubricate applicator well then gently insert applicator into the rectum. Thoroughly clean applicator and replace protective cover after each use.
- Regular use provides continual therapy for relief of symptoms

- also apply ointment to external area.

Other Information

- Store at room temperature 20º-25ºC (68º-77ºF)

Inactive Ingredients

Beeswax, Benzoic Acid, Cetyl alcohol, Glycerol Methylparaben, Polyoxyethylene lauryl ether, Propylparaben, Stearyl alcohol

Distributed by:

Distributed by RUGBY® LABORATORIES

17177 N. Laurel Park Drive, Suite 233

Livonia, MI. 48152

www.rugbylaboratories.com

Made in China

This Product is not manufactured or distributed by Pfizer Consumer Healthcare, distributor of Preparation H® Hemorrhoidal Ointment.

Questions or Comments?

1-800-645-2158